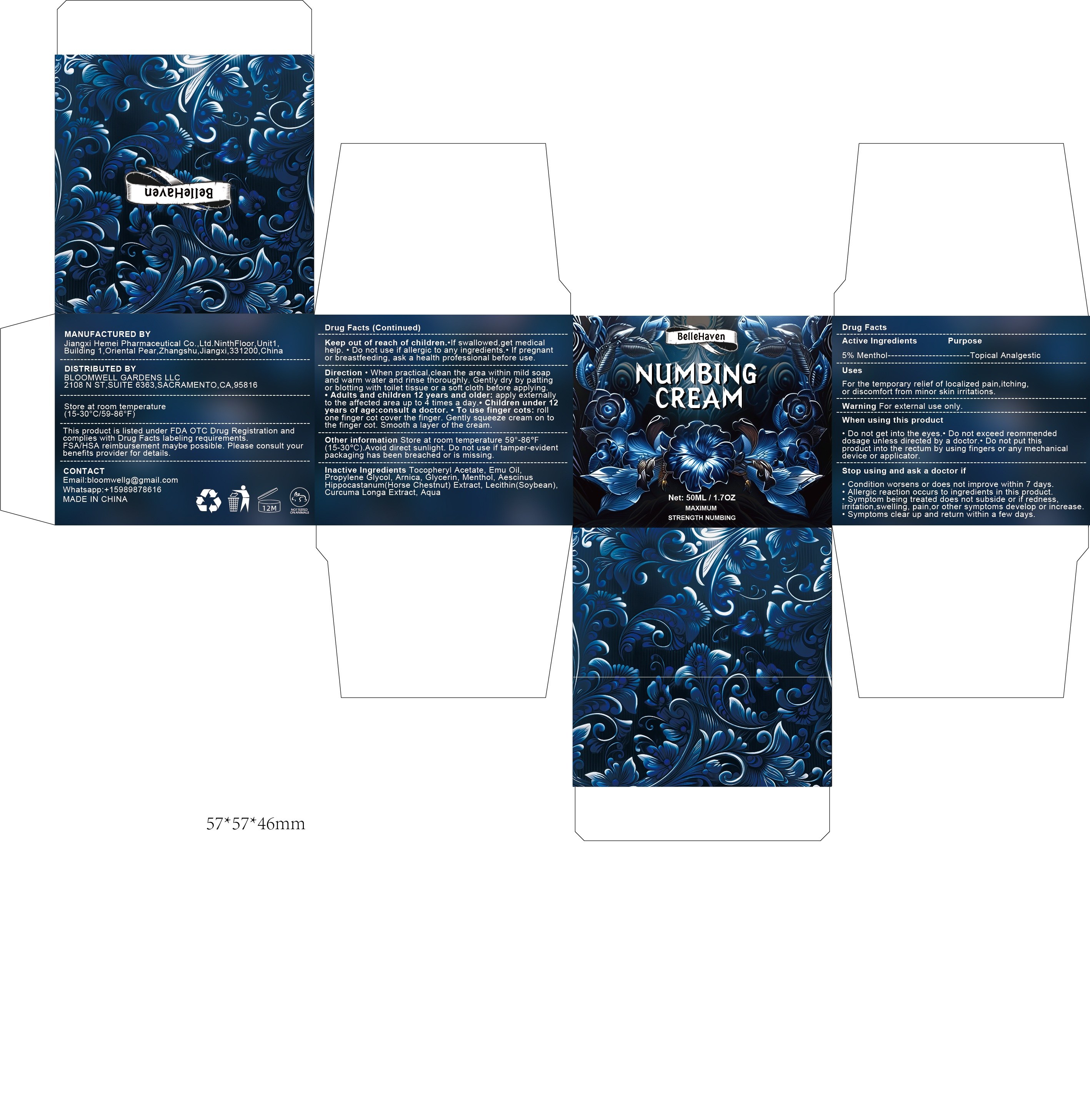 DRUG LABEL: Bellehaven numbing cream
NDC: 85284-009 | Form: CREAM
Manufacturer: BLOOMWELL GARDENS LLC
Category: otc | Type: HUMAN OTC DRUG LABEL
Date: 20250904

ACTIVE INGREDIENTS: MENTHOL 5 g/100 g
INACTIVE INGREDIENTS: SOYBEAN LECITHIN; EMU OIL; GLYCERIN; HORSE CHESTNUT; PROPYLENE GLYCOL; ARNICA MONTANA FLOWER WATER; ALPHA-TOCOPHEROL ACETATE; AQUA

Active Ingredients .......5% Menthol.

Inactive Ingredients
Tocopheryl Acetate, Emu Oil. Propylene Glycol, Arnica, Glycerin, Menthol, Aescinus Hippocastanum (Horse Chestnut)Extract, Lecithin(Soybean)Curcuma Longa Extract, Aqua

INDICATIONS AND USAGE

For the temporary relief of localized pain, itching or discomfort from minor skin irritations.

Warnings (For external use only)
For external use only

WHEN USING

·Do not get into the eyes.* Do not exceed recommended dosage unless directed by a doctor." Do not put this product into the rectum by using fingers or any mechanical device or applicator.

Stop using and ask a doctor if

Condition worsens or does not improve within 7 days
Allergic reaction occurs to ingredients in this product.
Symptom being treated does not subside or if redness irritation, swelling, pain, or other symptoms develop or increase
Symptoms clear up and return within a few days.

KEEP OUT OF REACH OF CHILDREN

lf swallowed, get medical help. Do not use if allergic to any ingredients.

PREGNANCY OR BREAST FEEDING

lf pregnant or breastfeeding, ask a health professional before use.

DOSAGE AND ADMINISTRATION

When practical, clean the area within mild soap and warm water and rinse thoroughly. Gently dry by patting or blotting with toilet tissue or a soft cloth before applying.
Adults and children 12 years and older: apply externally to the affected area up to 4 times a day.
Children under 12 years of age, consult a doctor.
To use finger cots: roll one finger cot cover the finger. Gently squeeze cream on to the finger cot. Smooth a layer of the cream.

OTHER SAFETY INFORMATION

Store at room temperature 59°-86°F（15-30°C）.Avoid direct sunlight. Do not use if tamper-evident packaging has been breached or is missing.

PURPOSE

Topical Analgesic